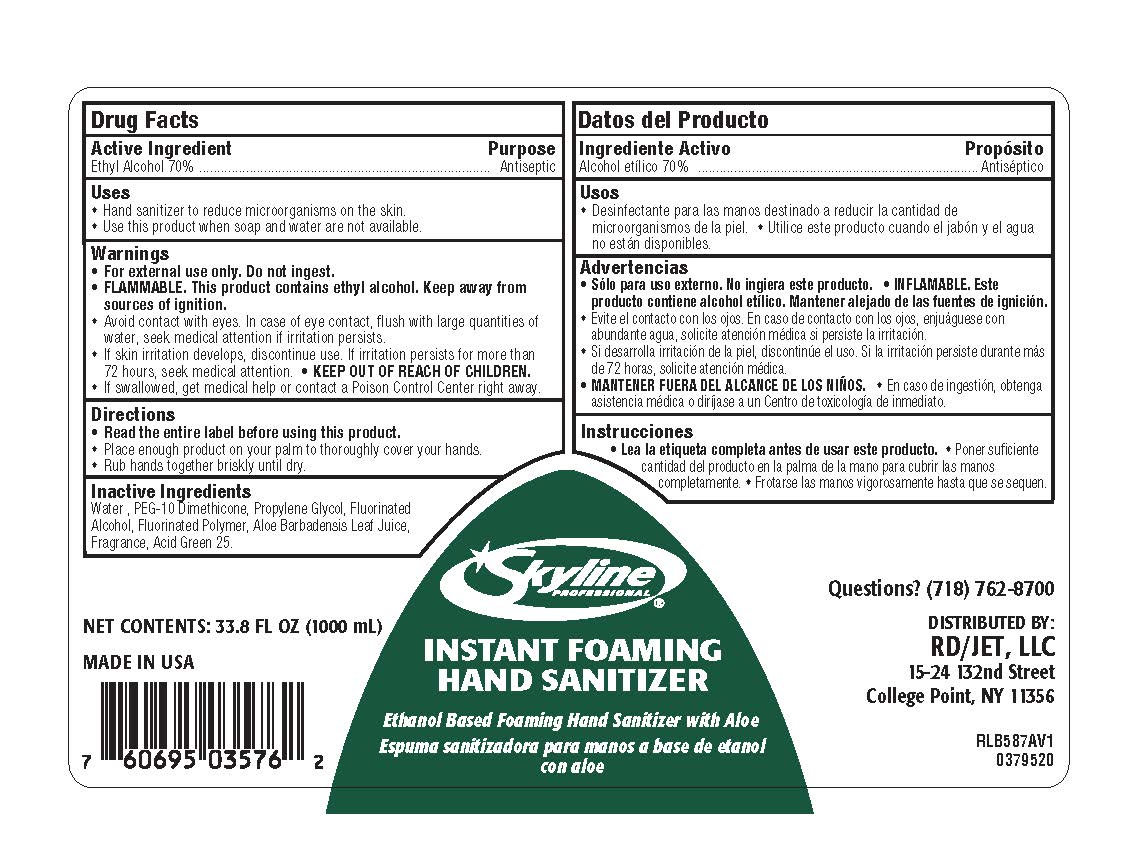 DRUG LABEL: Skyline Professional Instant Foaming Hand Sanitizer
NDC: 56131-800 | Form: SOAP
Manufacturer: RD Food Service DBA Restaurant Depot
Category: otc | Type: HUMAN OTC DRUG LABEL
Date: 20241209

ACTIVE INGREDIENTS: ALCOHOL 0.7 mL/1 mL
INACTIVE INGREDIENTS: BIS-PEG-12 DIMETHICONE (70 MPA.S); HEXYL ACETATE; HYDROXYCITRONELLAL; WATER; PROPYLENE GLYCOL; ALOE VERA LEAF; D&C GREEN NO. 5; TETRAHYDROLINALOOL; TETRAHYDROLINALYL ACETATE; ISOPROPYLPHENYLBUTANAL; 2-SEC-BUTYL CYCLOHEXANONE; CYCLOMETHICONE 4; EBANOL

Skyline Professional Instant Foaming Hand Sanitizer

Active Ingredient

Ethyl Alcohol 70%

Uses

- Use hand sanitizer to reduce microorganisms on the skin.
- Use this product when soap and water are not available.

Warnings

- For external use only. Do not ingest.
- FLAMMABLE. This product contains ethyl alcohol. Keep away from sources of ignition.
- Avoid contact with eyes. In case of eye contact, flush with large quantities of water, seek medical attention if irritation persists.
- If skin irritation develops, discontinue use. If irritation persists for more than 72 hours, seek medical attention.
- Keep out of reach of children.
- If swallowed, get medical help or contact a Poison Control Center right away

Directions

Read the entire label before using this product.

Place enough product on your palm to thoroughly cover your hands.

Rub hands together briskly until dry.

Inactive Ingredients

Water, PEG-10 Dimethicone, Propylene Glycol, Fluorinated Alcohol, Fluorinated Polymer, Aloe Barbadensis
Leaf Juice, Fragrance, Acid Green 25.

Purpose

Antiseptic

Skyline Professional Instant Foaming Hand Sanitizer

KEEP OUT OF REACH OF CHILDREN